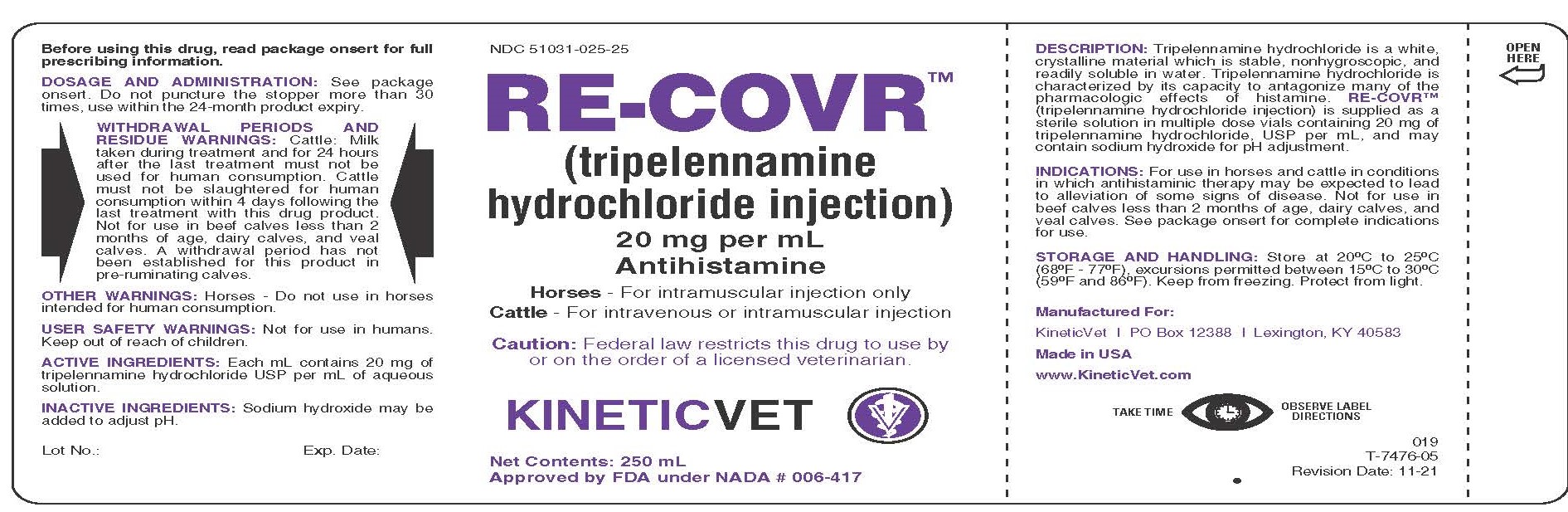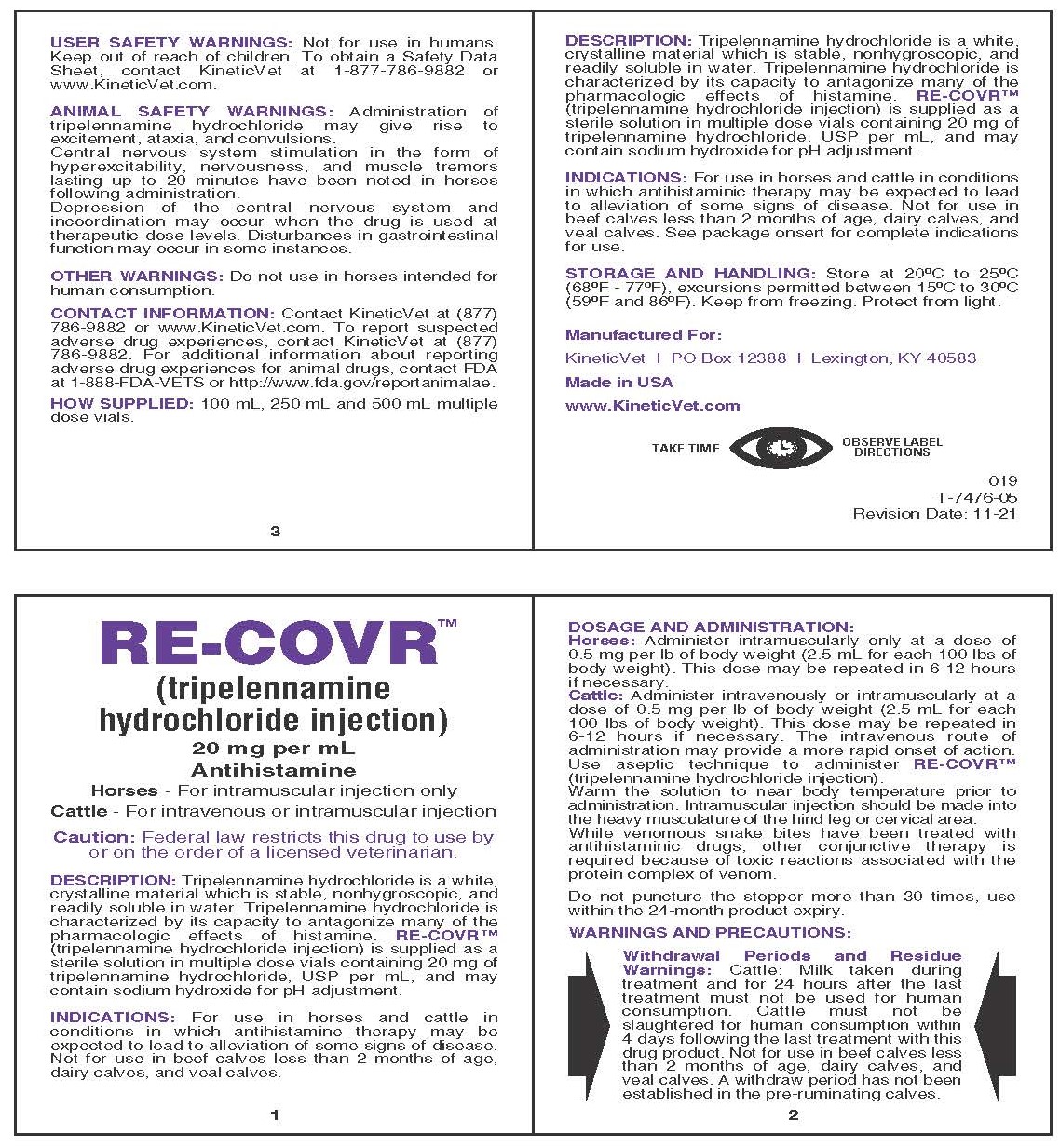 DRUG LABEL: RE-COVR
NDC: 51031-025 | Form: INJECTION
Manufacturer: Kinetic Technologies, LLC
Category: animal | Type: PRESCRIPTION ANIMAL DRUG LABEL
Date: 20220224

ACTIVE INGREDIENTS: TRIPELENNAMINE HYDROCHLORIDE 20 mg/1 mL

RE-COVR™ (tripelennamine hydrochloride injection) 20 mg per mL Antihistamine

DESCRIPTION:

Tripelennamine hydrochloride is a white, crystalline material which is stable, nonhygroscopic, and readily soluble in water. Tripelennamine hydrochloride is characterized by its capacity to antagonize many of the pharmacologic effects of histamine. RE-COVR™ (tripelennamine hydrochloride injection) is supplied as a sterile solution in multiple dose vials containing 20 mg of tripelennamine hydrochloride, USP per mL, and may contain sodium hydroxide for pH adjustment.

INDICATIONS:

For use in horses and cattle in conditions in which antihistaminic therapy may be expected to lead to alleviation of some signs of disease. Not for use in beef calves less than 2 months of age, dairy calves, and veal calves. See package onsert for complete indications for use.

DOSAGE AND ADMINISTRATION:

Horses: Administer intramuscularly only at a dose of 0.5 mg per lb of body weight (2.5 mL for each 100 lbs of body weight). This dose may be repeated in 6-12 hours if necessary.

Cattle: Administer intravenously or intramuscularly at a dose of 0.5 mg per lb of body weight (2.5 mL for each 100 lbs of body weight). This dose may be repeated in 6-12 hours if necessary. The intravenous route of administration may provide a more rapid onset of action. Use aseptic technique to administer RE-COVR™ (tripelennamine hydrochloride injection).

Warm the solution to near body temperature prior to administration. Intramuscular injection should be made into the heavy musculature of the hind leg or cervical area.

While venomous snake bites have been treated with antihistaminic drugs, other conjunctive therapy is required because of toxic reactions associated with the protein complex of venom.

Do not puncture the stopper more than 30 times, use within the 24-month product expiry.

STORAGE AND HANDLING:

Store at 20°C to 25°C (68°F - 77°F), excursions permitted between 15°C to 30°C (59°F and 86°F). Keep from freezing. Protect from light.

Manufactured For:

KineticVet, PO Box 12388, Lexington, KY 40538

Made in USA

www.KineticVet.com

TAKE TIME OBSERVE LABEL DIRECTIONS

Before using this drug, read package onsert for full prescribing information.

WITHDRAWAL PERIODS AND RESIDUE WARNINGS:

Cattle: Milk taken during treatment and for 24 hours after the last treatment must not be used for human consumption. Cattle must not be slaughtered for human consumption within 4 days following the last treatment with this drug product. Not for use in beef calves less than 2 months of age, dairy calves, and veal calves. A withdrawal period has not been established for this product in pre-ruminating calves.

ANIMAL SAFETY WARNINGS:

Administration of tripelennamine hydrochloride may give rise to excitement, ataxia, and convulsions.

Central nervous system stimulation in the form of hyperexcitability, nervousness, and muscle tremors lasting up to 20 minutes have been noted in horses following administration.

Depression of the central nervous system and incoordination may occur when the drug is used at therapeutic dose levels. Disturbances in gastrointestinal function may occur in some instances.

OTHER WARNINGS:

Horses - Do not use in horses intended for human consumption.

USER SAFETY WARNINGS:

Not for use in humans. Keep out of reach of children. To obtain a Safety Data Sheet, contact KineticVet at 1-877-786-9882 or www.KineticVet.com.

ACTIVE INGREDIENTS:

Each mL contains 20 mg of tripelennamine hydrochloride USP per mL of aqueous solution.

INACTIVE INGREDIENTS:

Sodium hydroxide may be added to adjust pH.

CONTACT INFORMATION:

Contact KineticVet at (877) 786-9882 or www.KineticVet.com. To report suspected adverse drug experiences, contact KineticVet at (877) 786-9882. For additional information about reporting adverse drug experiences for animal drugs, contact FDA at 1-888-FDA-VETS or http://www.fda.gov/reportanimalae.

HOW SUPPLIED:

100 mL, 250 mL and 500 mL multiple dose vials.

PACKAGE LABEL

NDC 51031-025-25

RE-COVR™ (tripelennamine hydrochloride injection)

20 mg per mL

Antihistamine

Horses - For intramuscular injection only

Cattle - For intravenous or intramuscular injection

Caution: Federal law restricts this drug to use by or on the order of a licensed veterinarian.

KINETICVET

Net Contents: 250 mL

Approved by FDA under NADA # 006-417